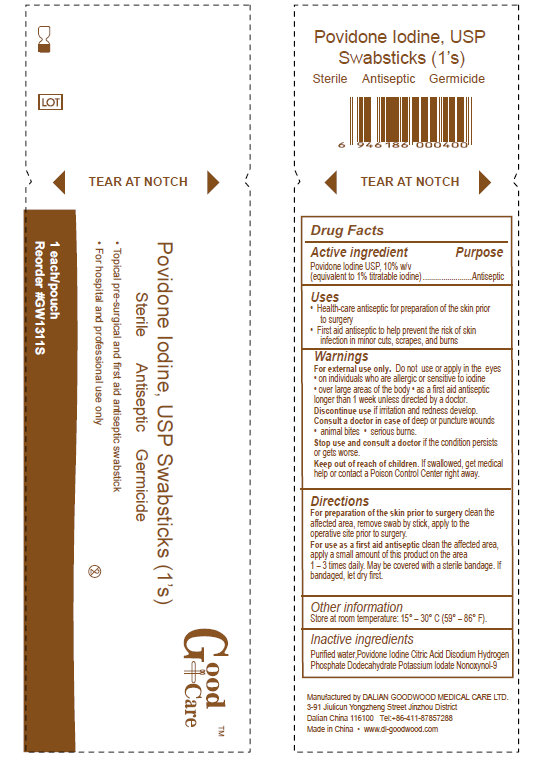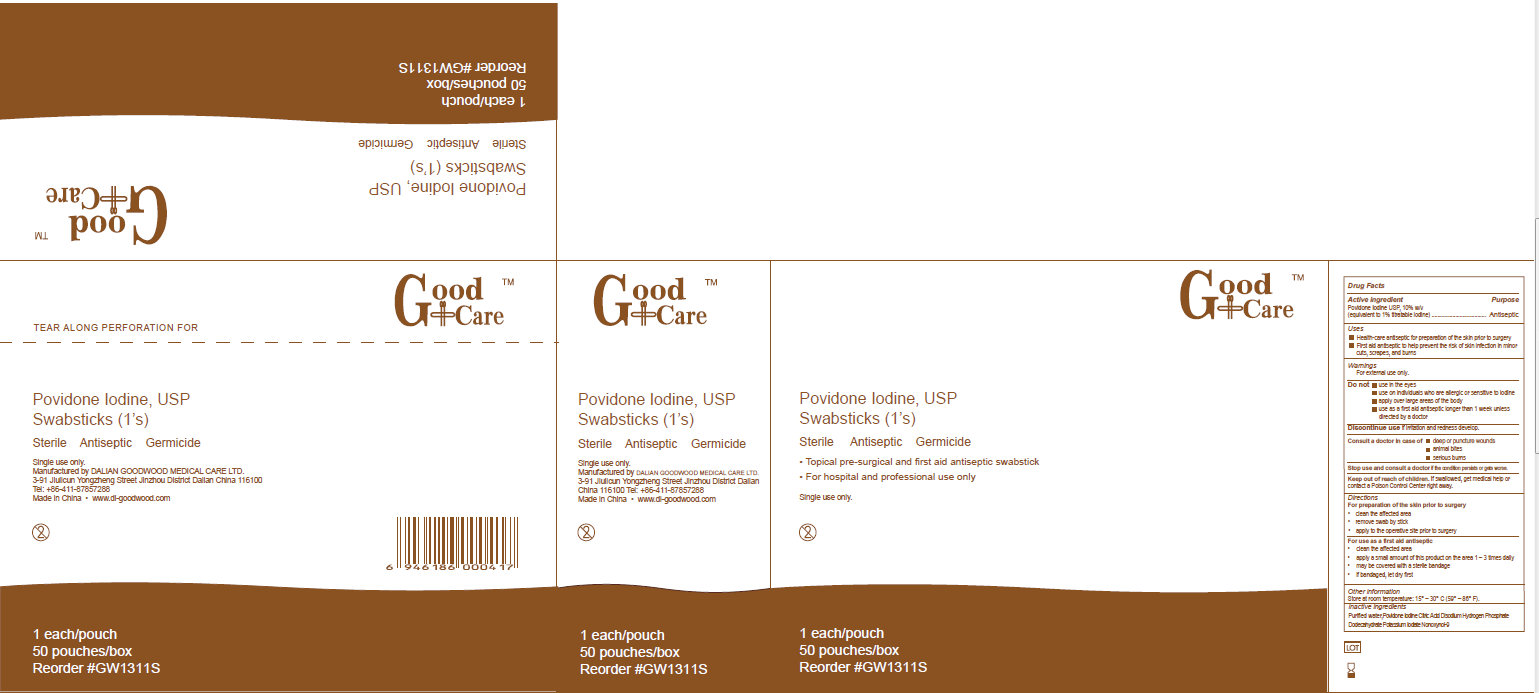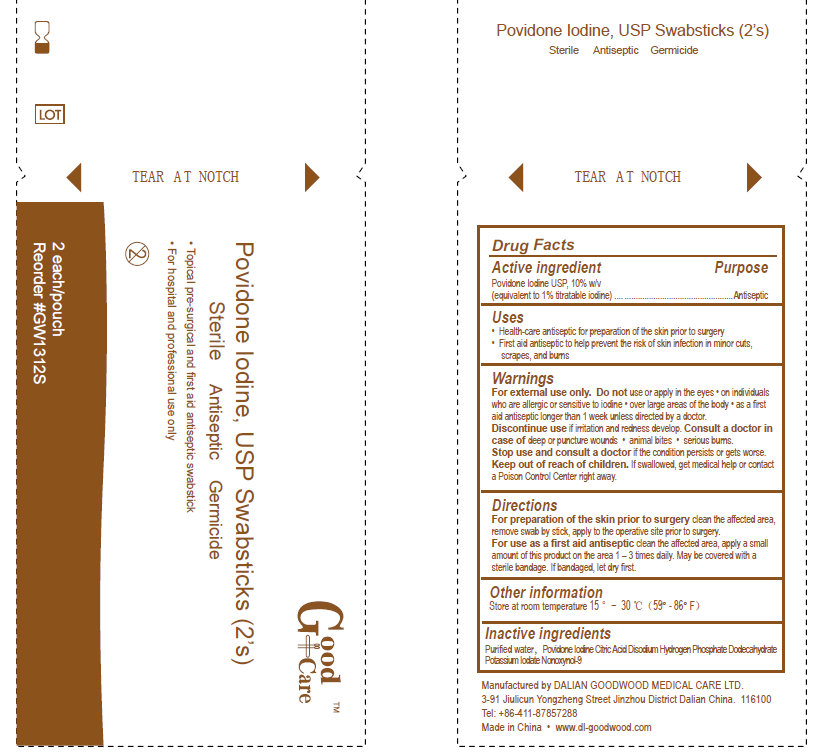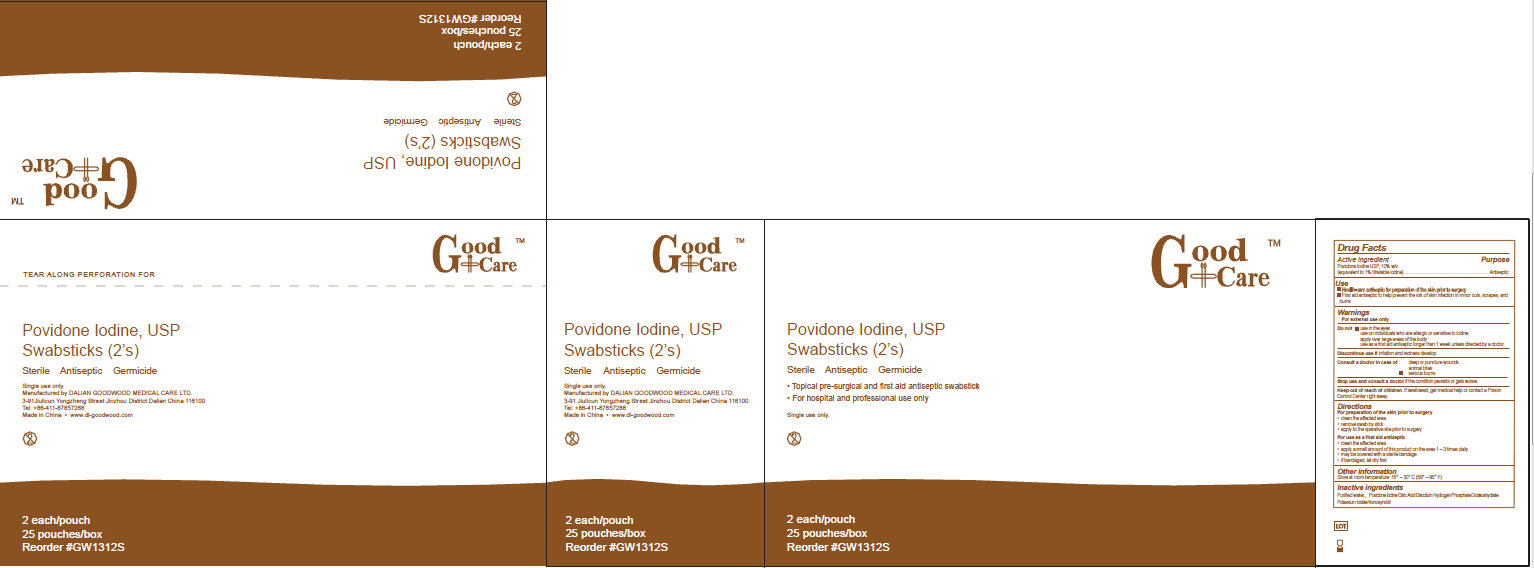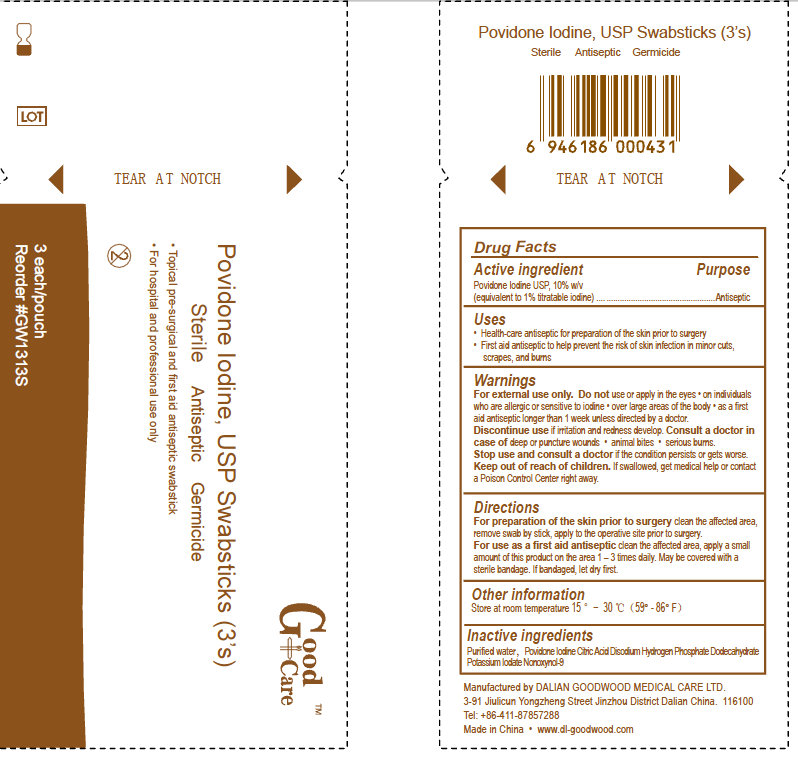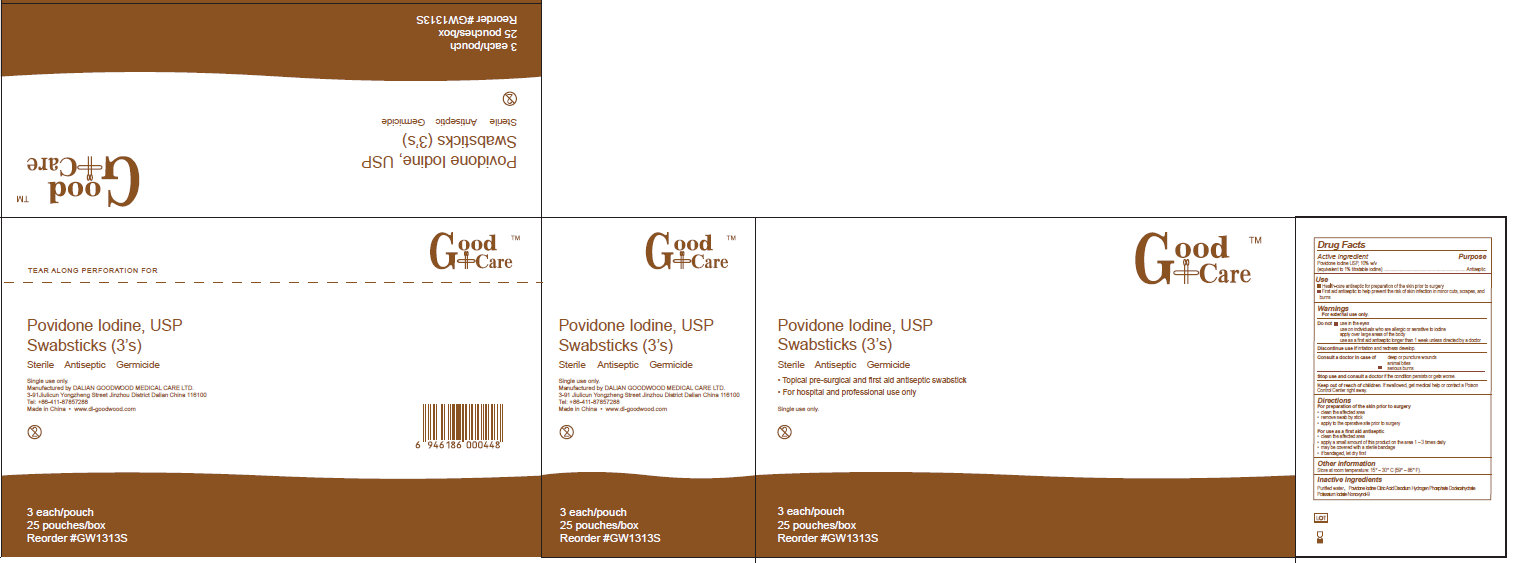 DRUG LABEL: Good Care Povidone Iodine Swabsticks
NDC: 50685-009 | Form: SWAB
Manufacturer: Dalian Goodwood Medical Care Ltd.
Category: otc | Type: HUMAN OTC DRUG LABEL
Date: 20230525

ACTIVE INGREDIENTS: POVIDONE-IODINE 10 g/100 g
INACTIVE INGREDIENTS: WATER; CITRIC ACID MONOHYDRATE; SODIUM PHOSPHATE, DIBASIC, DODECAHYDRATE; POTASSIUM IODATE

Good Care Povidone Iodine, USP Swabsticks

Active Ingredient

Povidone Iodine USP, 10%

Purpose

Antiseptic

Uses

- Health-care antiseptic for preparation of the skin prior to surgery
- First aid antiseptic to help prevent the risk of skin infection in minor cuts, scrapes, and burns

Warnings

For external use only. Do not use or apply in the eyes
on individuals who are allergic or sensitive to iodine
over large areas of the body
as a first aid antiseptic longer than 1 week unless directed by a doctor

Discontinue use if irritation and redness develop.

Consult a doctor in case of deep or puncture wounds, animal bites, serious burns.

Stop use and consult a doctor if the condition persists or gets worse.

Keep out of reach of children.

- If swallowed, get medical help or contact a Poison Control right away

Directions

For preparation of the skin prior to surgery clean the affected area, remove swab by stick, apply to the operative site prior to surgery

For use as a first aid antiseptic clean the affected area, apply a small amount of this product on the area 1-3 times daily. May be covered with a sterile bandage. If bandaged, let dry first.

Other Information

- Store at room temperature: 15 degrees - 30 degrees C (59 degrees - 86 degrees F)

Inactive Ingredients

Purified water, Povidone Iodine, Citric Acid Disodium Hydrogen Phosphate Dodecahydrate Potassium Iodate Nonoxynol

Manufactured by Dalian Goodwood Medical Care Ltd.

Made in China